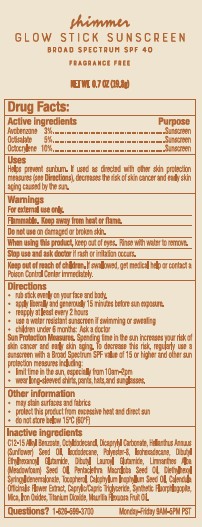 DRUG LABEL: TRADER JOES SHIMMER GLOW SUNSCREEN
NDC: 71270-162 | Form: STICK
Manufacturer: Trader Joe's Company
Category: otc | Type: HUMAN OTC DRUG LABEL
Date: 20250328

ACTIVE INGREDIENTS: AVOBENZONE 3 g/100 g; OCTISALATE 5 g/100 g; OCTOCRYLENE 10 g/100 g
INACTIVE INGREDIENTS: CALENDULA OFFICINALIS FLOWER; MAGNESIUM POTASSIUM ALUMINOSILICATE FLUORIDE; MICA; TITANIUM DIOXIDE; MAURITIA FLEXUOSA FRUIT OIL; C12-15 ALKYL BENZOATE; OCTYLDODECANOL; DICAPRYLYL CARBONATE; SUNFLOWER OIL; ISODODECANE; POLYESTER-8 (1400 MW, CYANODIPHENYLPROPENOYL CAPPED); ISOHEXADECANE; DIBUTYL ETHYLHEXANOYL GLUTAMIDE; DIBUTYL LAUROYL GLUTAMIDE; LIMNANTHES ALBA (MEADOWFOAM) SEED OIL; PENTACLETHRA MACROLOBA SEED OIL; DIETHYLHEXYL SYRINGYLIDENEMALONATE; TOCOPHEROL; TAMANU OIL; MEDIUM-CHAIN TRIGLYCERIDES; FERRIC OXIDE RED

TRADER JOE’S (as PLD) - Shimmer Glow Stick Sunscreen SPF 40 (71270-162)

ACTIVE INGREDIENTS

AVOBENZONE 3%

OCTISALATE 5%

OCTOCRYLENE 10%

PURPOSE

SUNSCREEN

USES

HELPS PREVENT SUNSCREEN. IF USED AS DIRECTED WITH OTHER SUN PROTECTION MEASURES (SEE DIRECTIONS), DECREASES THE RISK OF SKIN CANCER AND EARLY SKIN AGING CAUSED BY THE SUN.

WARNINGS

For external use only.

Flammable. Keep away from heat or flame. Do not use on damaged or broken skin.

When using this product, keep out of eyes. Rinse with water to remove.

Stop use and ask doctor if rash or irritation occurs.

Keep out of reach of children.If swallowed, get medical help or contact a Poison Control Center immediately.

DIRECTIONS

- Apply liberally to face and body 15 minutes before sun exposure.
- Reapply: after 80 minutes of swimming or sweating
- immediately after towel drying
- at least every 2 hours.
- Children under 6 months: ask a doctor.

Sun Protection Measures.Spending time in the sun increases your risk of skin cancer and early skin aging. To decrease this risk, regularly use a sunscreen with a Broad Spectrum SPF 15 value or higher along with other sun protection measures including:

- limit time in the sun, especially from 10 a.m. – 2 p.m.
- wear long sleeved shirts, pants, hats and sunglasses.

OTHER INFORMATION

- Protect the product in this container from excessive heat and direct sun
- May stain surfaces and fabrics.

INACTIVE INGREDIENTS

WATER (AQUA), GLYCERIN, CYCLOPENTASILOXANE, C12-15 ALKYL BENZOATE, VP/HEXADECENE COPOLYMER, PHENOXYETHANOL, ETHYLHEXYLGLYCERIN, SODIUM BENZOATE, SODIUM HYDROXIDE, POTASSIUM SORBATE, DISODIUM EDTA, ASCORBIC ACID, TOCOPHERYL ACETATE.

QUESTIONS OR COMMENTS?

1- 626-599-3700Monday – Friday 9 AM – 5 PM PST